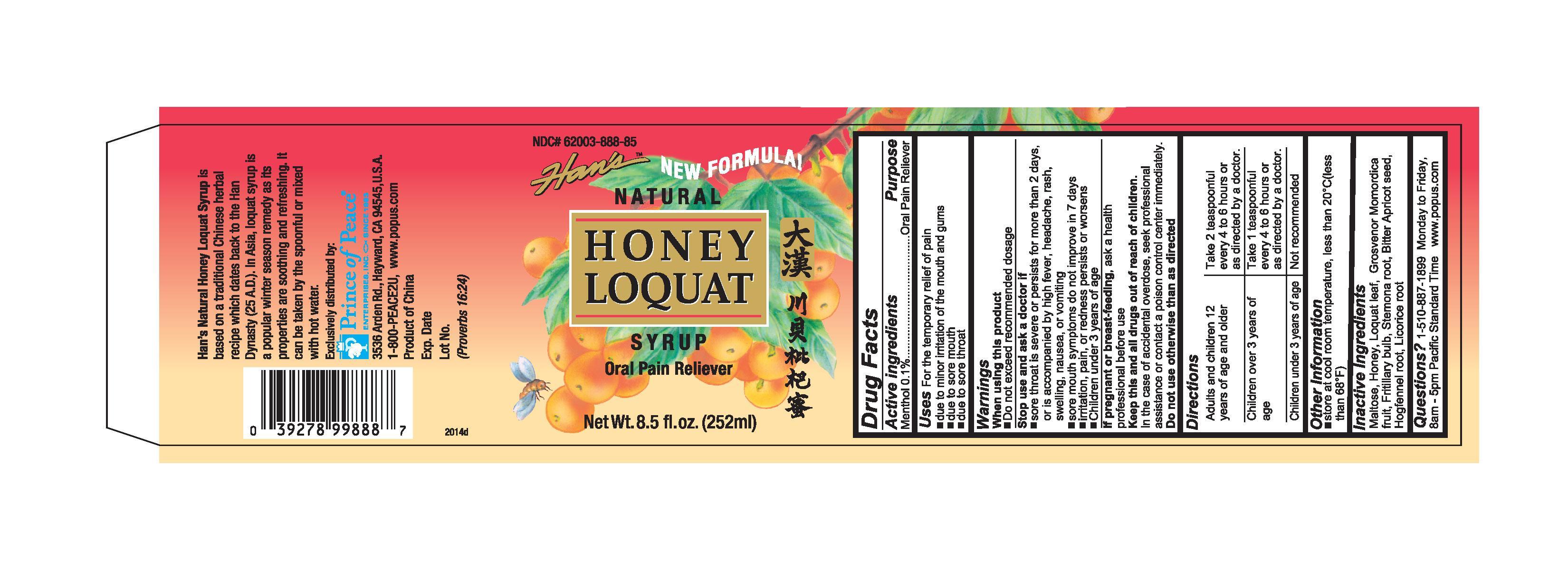 DRUG LABEL: Han Honey Loquat Syrup
NDC: 62003-888 | Form: SYRUP
Manufacturer: PRINCE OF PEACE ENTERPRISES INC.
Category: otc | Type: HUMAN OTC DRUG LABEL
Date: 20140426

ACTIVE INGREDIENTS: MENTHOL 0.1 g/100 mL
INACTIVE INGREDIENTS: MALTOSE; HONEY; ERIOBOTRYA JAPONICA LEAF; SIRAITIA GROSVENORII FRUIT; FRITILLARIA CIRRHOSA BULB; STEMONA SESSILIFOLIA ROOT; PEUCEDANUM PRAERUPTORUM ROOT; GLYCYRRHIZA GLABRA; PRUNUS ARMENIACA SEED; MENTHA ARVENSIS LEAF

Han’s Honey Loquat Syrup

ACTIVE INGREDIENT

- Menthol 0.1%......................................Oral Pain Reliever

INDICATIONS AND USAGE

Uses For the temporary relief of pain

- due to minor irritation of the mouth and gumsdue to minor irritation of the mouth and gums

- due to sore mouth

- due to sore throat

WARNINGS

WHEN USING

- Do not exceed recommended dosage

Stop use and ask a doctor if

- sore throat is severe or persists for more than 2 days, or is accompanied by high fever, headache, rash, swelling, nausea, or vomiting

- sore mouth symptoms do not improve in 7 days

- irritation, pain, or redness persists or worsens

- Children under 3 years of age

- Do not use otherwise than as directed

KEEP OUT OF REACH OF CHILDREN

- Keep this and all drugs out of reach of children.

- In the case of accidental overdose, seek professional assistance or contact a poison control center immediately.

PREGNANCY OR BREAST FEEDING

- If pregnant or breast-feeding, ask a health professional before use.

Directions

Adults and children 12 years of age and older | Take 2 teaspoonful every 4 to 6 hours or as directed by a doctor.
Children over 3 years of age | Take 1 teaspoonful every 4 to 6 hours or as directed by a doctor.
Children under 3 years of age | Not recommended

OTHER SAFETY INFORMATION

- store at cool room temperature, less than 20°C (less than 68°F)

QUESTIONS

- -510-887-1899 Monday to Friday, 8am - 5pm Pacific Standard Time
- www.popus.com

INACTIVE INGREDIENT

- Maltose, Honey, Loquat leaf, Grosvenor Momordica fruit, Fritillary bulb, Stemona root, Bitter Apricot seed, Hogfennel root, Licorice root